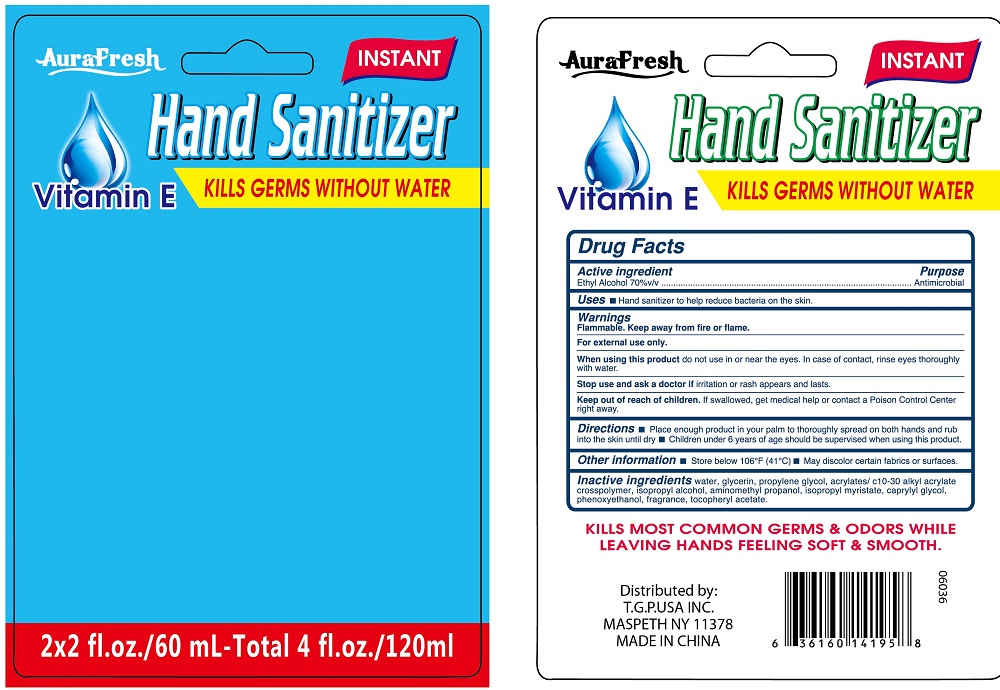 DRUG LABEL: aurafresh instant hand sanitizer
NDC: 40104-284 | Form: GEL
Manufacturer: Ningbo Pulisi Daily Chemical Products Co., Ltd.
Category: otc | Type: HUMAN OTC DRUG LABEL
Date: 20170810

ACTIVE INGREDIENTS: alcohol 70 mL/100 mL
INACTIVE INGREDIENTS: WATER; PROPYLENE GLYCOL; ALOE VERA LEAF; CARBOMER 934; GLYCERIN; .ALPHA.-TOCOPHEROL ACETATE, D-; TROLAMINE; CARBOMER COPOLYMER TYPE A; ISOPROPYL ALCOHOL; AMINOMETHYLPROPANOL; CAPRYLYL GLYCOL; PHENOXYETHANOL

Drug facts

Active ingredient Purpose

Ethyl Alcohol 70% ... Antiseptic

PURPOSE

Hand sanitizer to help decrease bacteria on the skin.

KEEP OUT OF REACH OF CHILDREN

If swallowed, get medical help or contact local poison control center right away.

Children under 6 years of age should be supervised when using this product.

INDICATIONS AND USAGE

keep out of eyes

when water, soap and towel are not available

WARNINGS

For external use only.
Flammable. Keep away from hear or flame.

When using this products, do not use in or the eyes. In case of contact, rinse eyes thoroughly with water.

Stop using and ask a doctor, if irritation or rash appears and lasts.

DOSAGE AND ADMINISTRATION

place enough product in your palms to thoroughly spread on both hands, and rub into the skin until dry.

INACTIVE INGREDIENT

Water, Carbomer, Glycerin, Propylene Glycol, Triethanolamine, acrylates/c10-30 alkyl acrylate crosspolymer, isopropyl alcohol, aminomethyl propanol, isopropyl mysistate, caprylyl glycol, phenoxyethanol, Tocopheryl Acetate, Fragrance